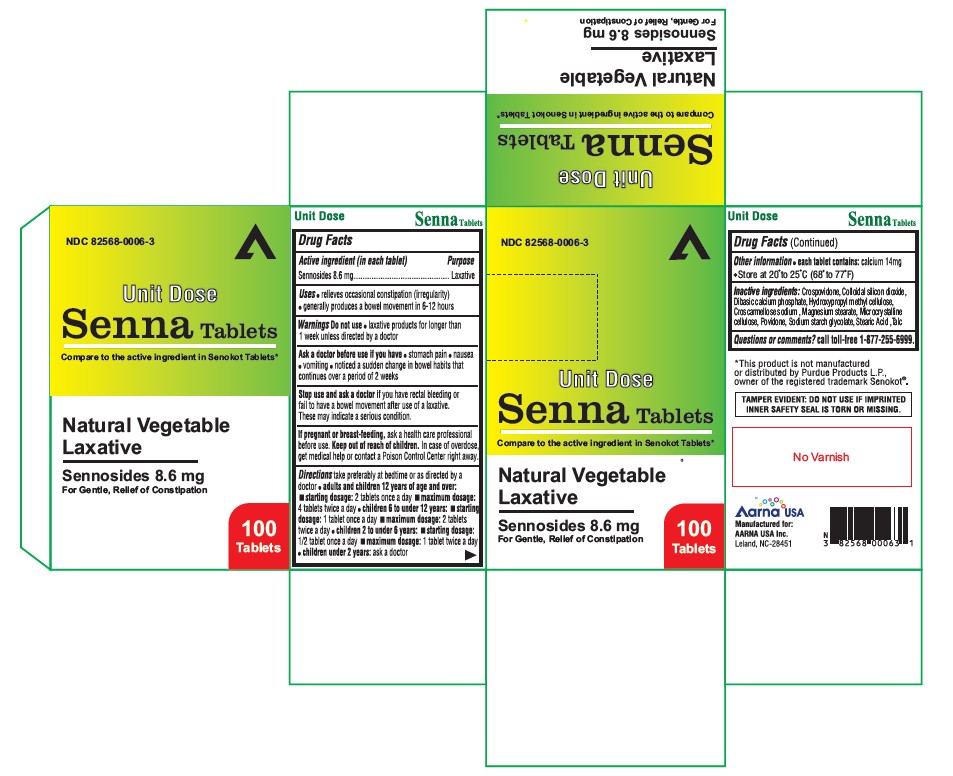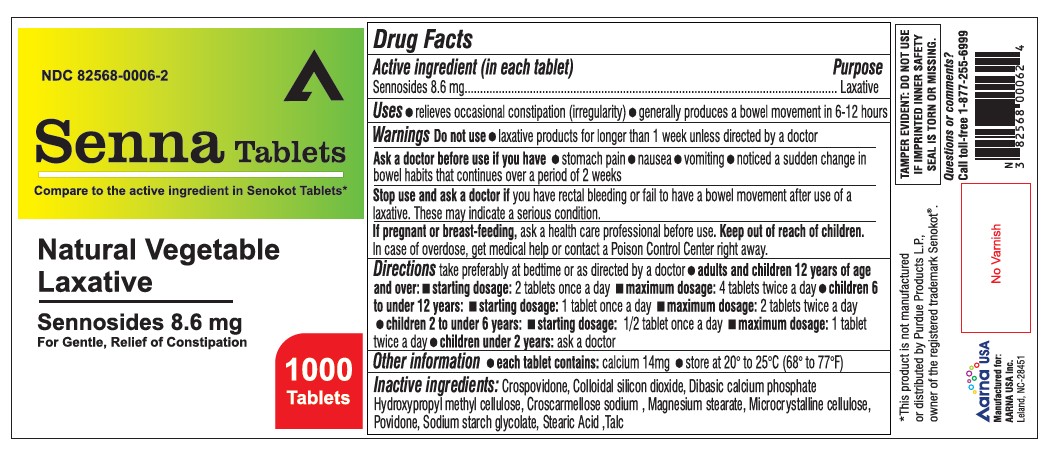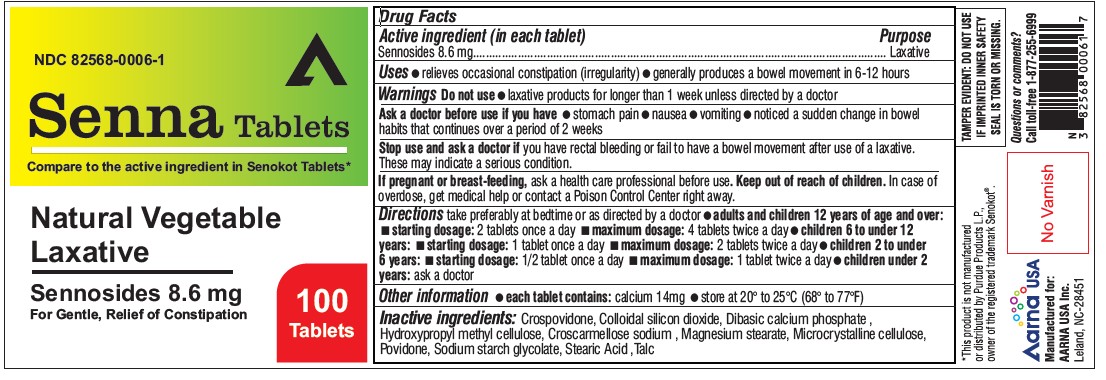 DRUG LABEL: SENNA
NDC: 82568-0006 | Form: TABLET
Manufacturer: AARNA USA INC.
Category: otc | Type: HUMAN OTC DRUG LABEL
Date: 20250529

ACTIVE INGREDIENTS: SENNOSIDES 8.6 mg/1 1
INACTIVE INGREDIENTS: CROSPOVIDONE; SILICON DIOXIDE; CALCIUM PHOSPHATE, DIBASIC, ANHYDROUS; HYDROXYPROPYL METHYLCELLULOSE; CROSCARMELLOSE SODIUM; MAGNESIUM STEARATE; MICROCRYSTALLINE CELLULOSE; POVIDONE; SODIUM STARCH GLYCOLATE TYPE A CORN; STEARIC ACID; TALC

Senna Tablets
Natural Vegitable Lexative

Drug Facts

Active ingredient (in each tablet)

Sennosides 8.6 mg

Purpose

Laxative

Uses

- relieves occasional constipation (irregularity)
- generally causes a bowel movement in 6-12 hours

Do not use

- laxative products for longer than one week unless directed by a doctor

Do not use

laxative products for longer than one week unless directed by a doctor

Ask a doctor before use if you have

- stomach pain
- nausea
- vomiting
- noticed a sudden change in bowel habits that continues over a period of 2 weeks

Stop use and ask a doctor if

you have rectal bleeding or fail to have a bowel movement after use of a laxative.

These may indicate a serious condition.

If pregnant or breast-feeding,

ask a health care professional before use.

OVERDOSAGE

In case of overdose, get medical help or contact a Poison Control Center right away.

Directions

take preferably at bedtime or as directed by a doctor

age | starting dosage | maximum dosage
Adults and children; 12 years of age and older | 2 tablets; once a day | 4 tablets; twice a day
Children 6 to under; 12 years of age | 1 tablet; once a day | 2 tablets; twice a day
Children 2 to under; 6 years of age | 1/2 tablet; once a day | 1 tablet; twice a day
Children under; 2 years of age | ask a doctor | ask a doctor

Other information

- Each tablet contains: Calcium 14 mg
- Store between 15º to 30ºC (59 to 86F)

Inactive ingredients

microcrystaline cellulose, dicalcium phosphate, sodium starch glycolate, croscarmellose sodium, hypromellose, povidone, collodial silicon dioxide, megnesium stearate.

Questions or comments?

1-(877) 255-6999

Tamper Evident:

Do not use if imprinted inner safety seal is torn or missing.

This product is not manufactured or distributed by Purdue Products L.P.,

Owner of the registered trademark Senokot®

Manufactured for:

Aarna USA Inc.

Leland, NC 28451